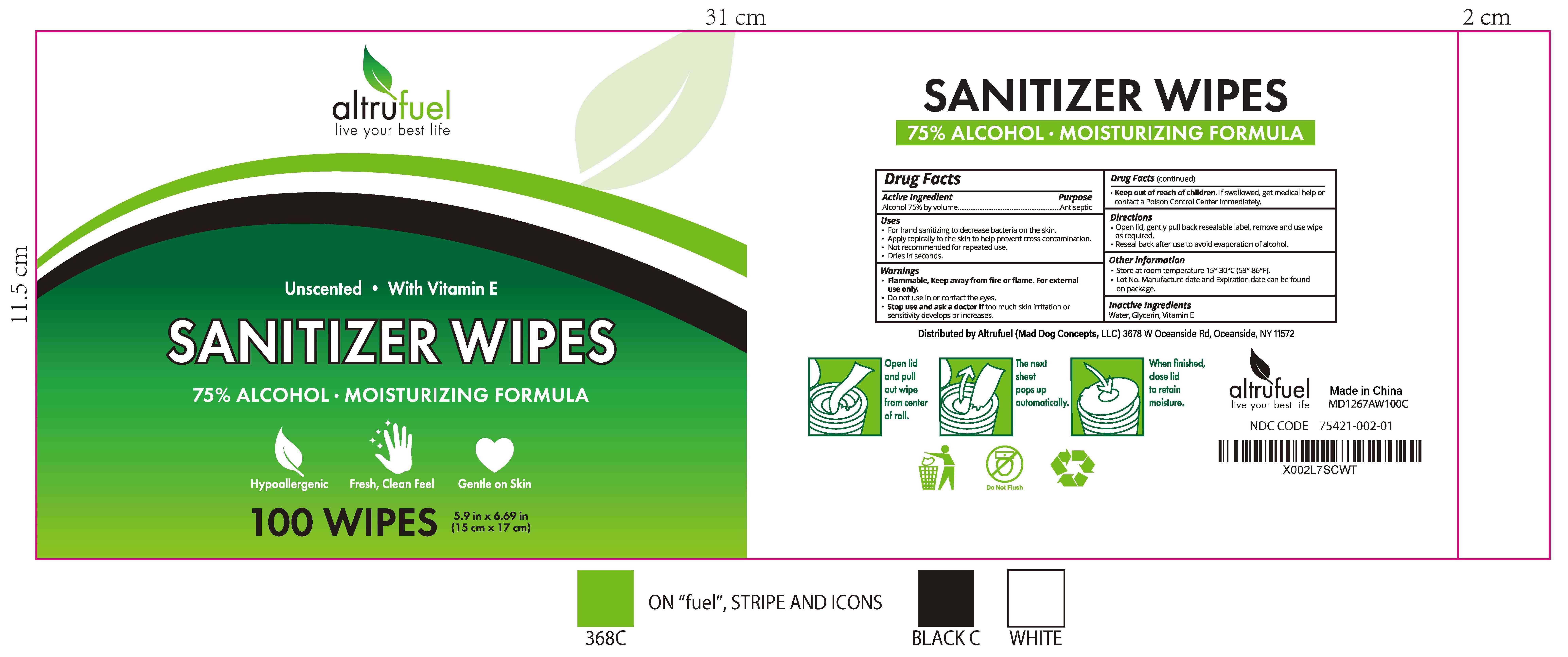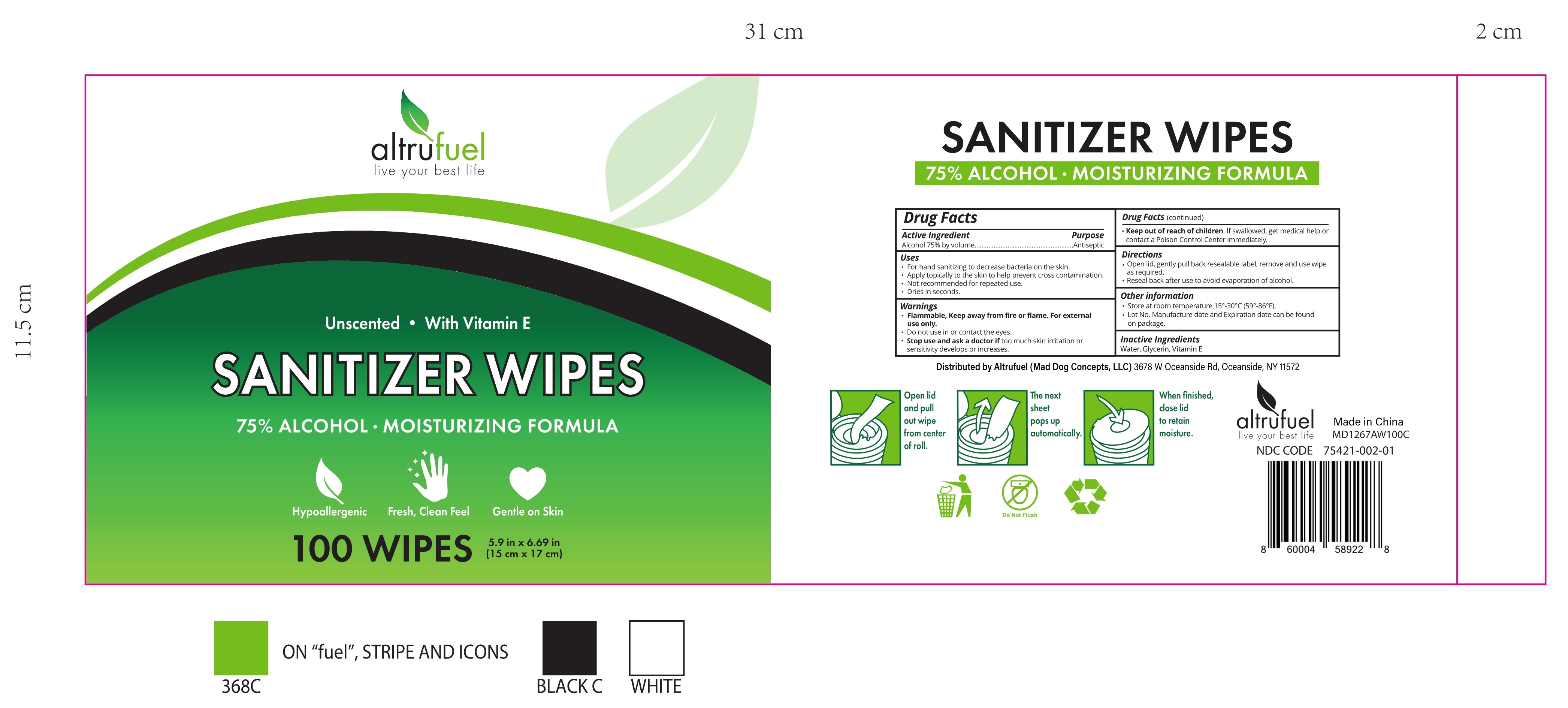 DRUG LABEL: SANITIZER WIPES
NDC: 74763-015 | Form: CLOTH
Manufacturer: ZHEJIANG GAFLE AUTO CHEMICAL CO.,LTD
Category: otc | Type: HUMAN OTC DRUG LABEL
Date: 20220328

ACTIVE INGREDIENTS: ALCOHOL 75 mL/100 1
INACTIVE INGREDIENTS: WATER; .ALPHA.-TOCOPHEROL; GLYCERIN

015覆盖014 SANITIZER WIPES

ACTIVE INGERDIENT

Alcohol 75% by volume

PURPOSE

Antimicrobial

USES

For hand sanitizing to decrease bacteria on the skin.
Apply topically to the skin to help prevent cross contamination.
Not recommended for repeated use.
Dries in seconds.

WARNINGS

Flammable, Keep away from fire or flame. For external use only.

Do not use in or contact the eyes.

Stop use and ask a doctor if too much skin irritation or sensitivity develops or increases.

Keep out of reach of children. If swallowed, get medical help or contact a Poison Control Center immediately.

Do not use in or contact the eyes.

Do not use in or contact the eyes.

Stop use and ask a doctor if too much skin irritation or sensitivity develops or increases.

Keep out of reach of children. If swallowed, get medical help or contact a Poison Control Center immediately.

Stop use and ask a doctor if too much skin irritation or sensitivity develops or increases.

Keep out of reach of children. If swallowed, get medical help or contact a Poison Control Center immediately.

DIRECTIONS

Open lid, gently pull back resealable label, remove and use wipe as required.
Reseal back after use to avoid evaporation of alcohol.

OTHER INFORMATION

Store at room temperature 15°-30° C (59°-86° F).
Lot No. Manufacture date and Expiration date can be found on package.

INACTIVE INGERDIENTS

Water, Glycerin, Vitamin E